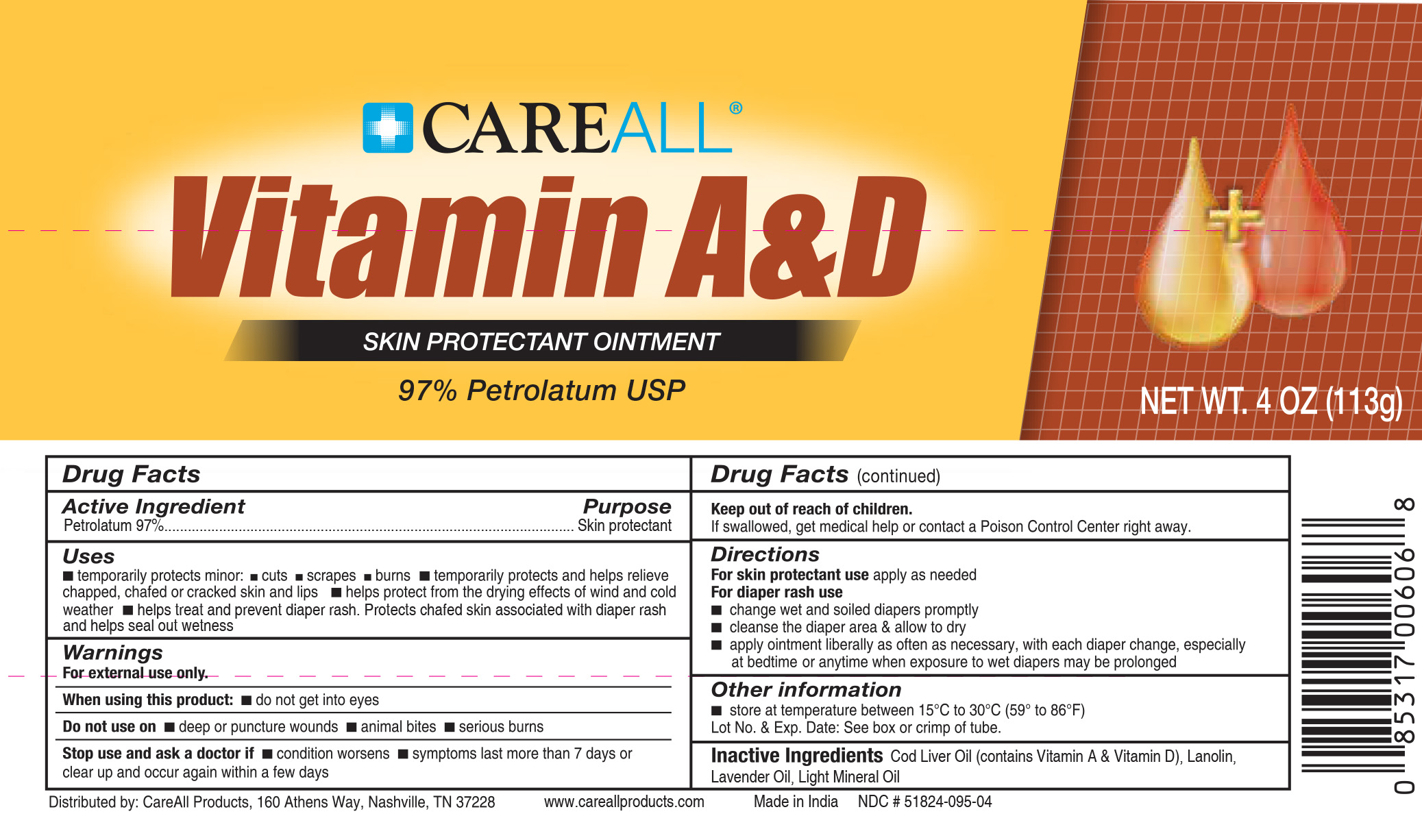 DRUG LABEL: CAREALL Vitamin A and D
NDC: 51824-095 | Form: OINTMENT
Manufacturer: New World Imports, Inc
Category: otc | Type: HUMAN OTC DRUG LABEL
Date: 20251201

ACTIVE INGREDIENTS: PETROLATUM 0.97 g/1 g
INACTIVE INGREDIENTS: LAVENDER OIL; COD LIVER OIL; LANOLIN; LIGHT MINERAL OIL

DRUG FACTS

ACTIVE INGREDIENT

White Petrolatum 97%

PURPOSE

Skin Protectant

Keep out of reach of children.If swallowed, get medical help or contact a Poison Control Center right away.

INDICATIONS AND USAGE

Temporarily protects minor cuts, scrapes and burns

Temporarily protects and helps relieve chapped, chafed or cracked skin and lips

Helps protect from the drying effects of wind and cold weather

Helps treat and prevent diaper rash. Protects chafed skin associated with diaper rash and helps seal out wetness

WARNINGS

For external use only.

When using this productdo not get into eyes

Do not use on:

Deep or puncture wounds

Animal bites

Serious burns

Stop use and ask a doctor if:

Condition worsens

Symptoms last more than 7 days or clear up and occur again within a few days

DOSAGE AND ADMINISTRATION

For skin protectant useapply as needed

For diaper rash use:

Change wet and soiled diapers promptly

Cleanse the diaper area and allow to dry

Apply ointment liberally as often as necessary, with each diaper change, especially at bedtime or anytime when exposure to wet diapers may be prolonged

INACTIVE INGREDIENT

Cod Liver Oil (Contains Vitamin A and D), Lanolin, Lavendar Oil, Light Liquid Paraffin, Liquid Paraffin, Vitamin A, Vitamin D, White Petolatum